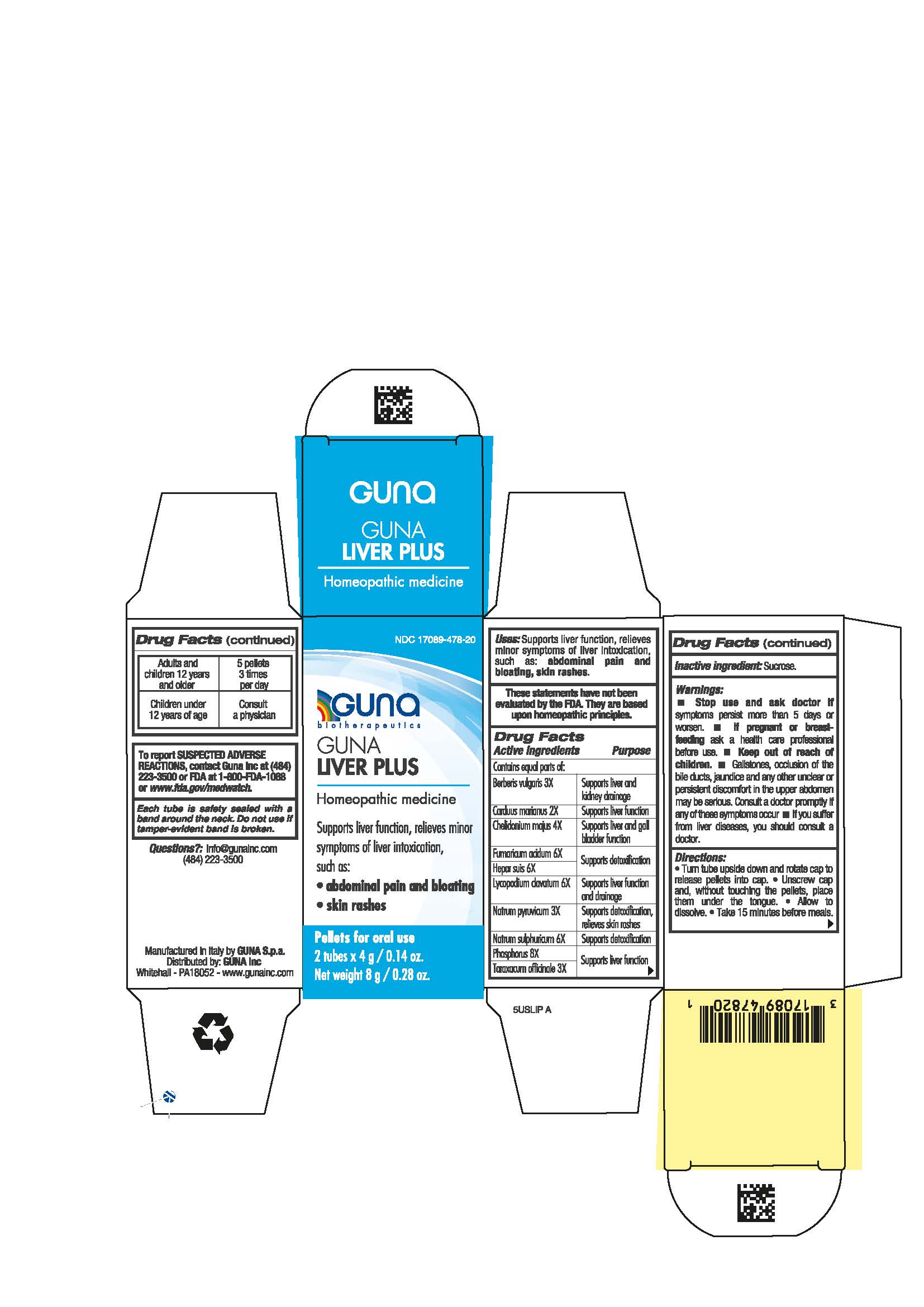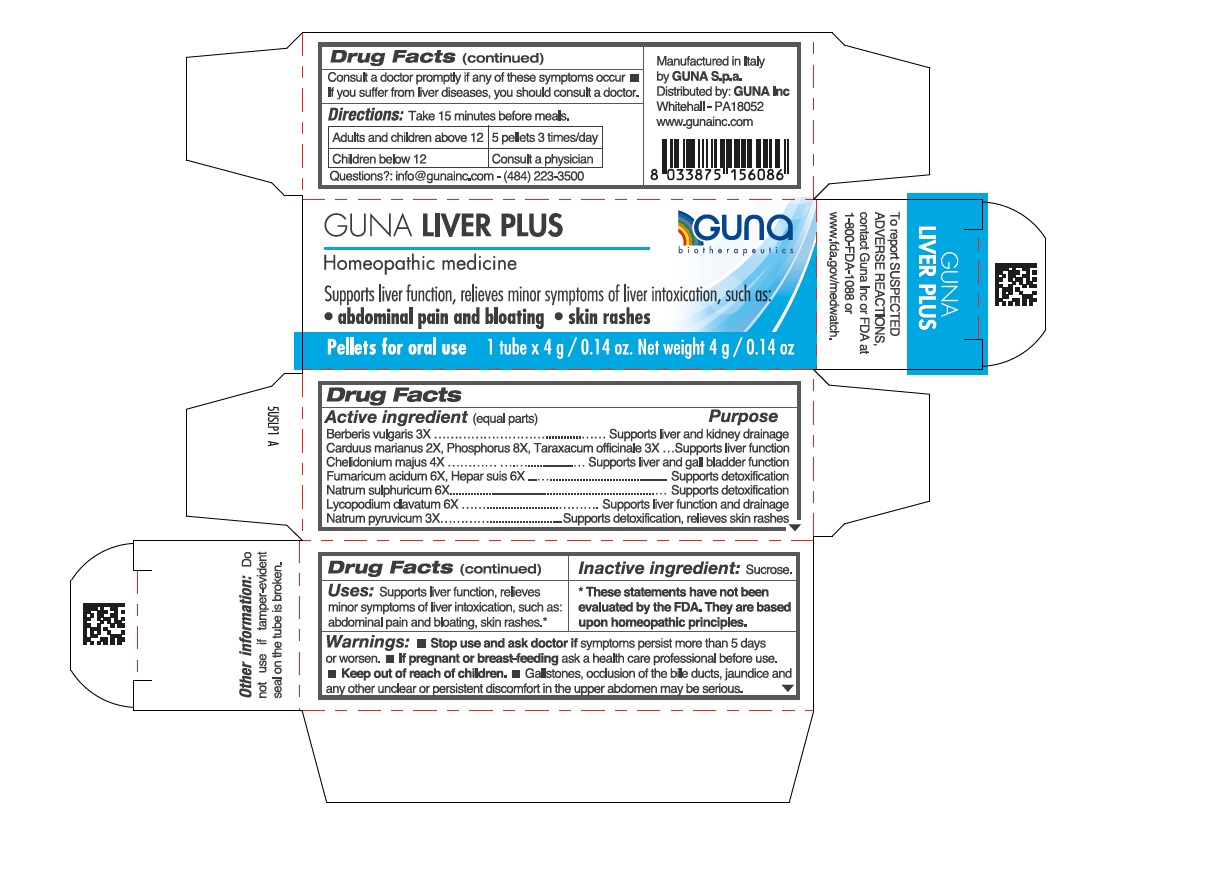 DRUG LABEL: GUNA LIVER PLUS
NDC: 17089-478 | Form: PELLET
Manufacturer: Guna spa
Category: homeopathic | Type: HUMAN OTC DRUG LABEL
Date: 20211215

ACTIVE INGREDIENTS: SILYBUM MARIANUM SEED 2 [hp_X]/4 g; CHELIDONIUM MAJUS 4 [hp_X]/4 g; FUMARIC ACID 6 [hp_X]/4 g; PORK LIVER 6 [hp_X]/4 g; SODIUM PYRUVATE 3 [hp_X]/4 g; LYCOPODIUM CLAVATUM SPORE 6 [hp_X]/4 g; SODIUM SULFATE 6 [hp_X]/4 g; PHOSPHORUS 8 [hp_X]/4 g; BERBERIS VULGARIS ROOT BARK 3 [hp_X]/4 g; TARAXACUM OFFICINALE 3 [hp_X]/4 g
INACTIVE INGREDIENTS: SUCROSE

GUNA LIVER PLUS

Inactive ingredient: Sucrose.

Questions?: info@gunainc.com
tel. (484) 223-3500

INDICATIONS AND USAGE

Turn tube upside down and rotate cap to release pellets into cap.
Unscrew cap and without touching pellets tip them into the mouth under the tongue.
Allow to dissolve
Take 15 minutes before meals.

DOSAGE AND ADMINISTRATION

Adults and children 12 years and older 5 pellets 3 times per day
Children under 12 years of age consult a physician

Keep out of reach of children

PREGNANCY OR BREAST FEEDING

If pregnant or breast-feeding ask a health care professional before use.

Stop use and ask doctor if symptoms persist more than 5 days or worsen.
If pregnant or breast-feeding ask a health care professional before use.
Keep out of reach of children.

Gallstones, occlusion of the bile ducts, jaundice and any other unclear or persistent discomfort in the upper abdomen may be serious. Consult a doctor promptly if any of these symptoms occur

If you suffer from liver diseases, you should consult a doctor

PURPOSE

Supports liver function, relieves minor symptoms of liver intoxication, such as:

- abdominal pain and bloating
- skin rashes

ACTIVE INGREDIENT

Berberis vulgaris 3X Supports liver and kidney drainage

Carduus marianus 2X Supports liver function

Chelidonium majus 4X Supports liver and gall bladder function

Fumaricum acidum 6X Supports detoxification

Hepar suis 6X Supports detoxification

Lycopodium clavatum 6X Supports liver function and drainage

Natrum pyruvicum 3X Supports detoxification, relieves skin rashes

Natrum sulphuricum 6X Supports detoxification

Phosphorus 8X Supports liver function

Taraxacum officinale 3X Supports liver function